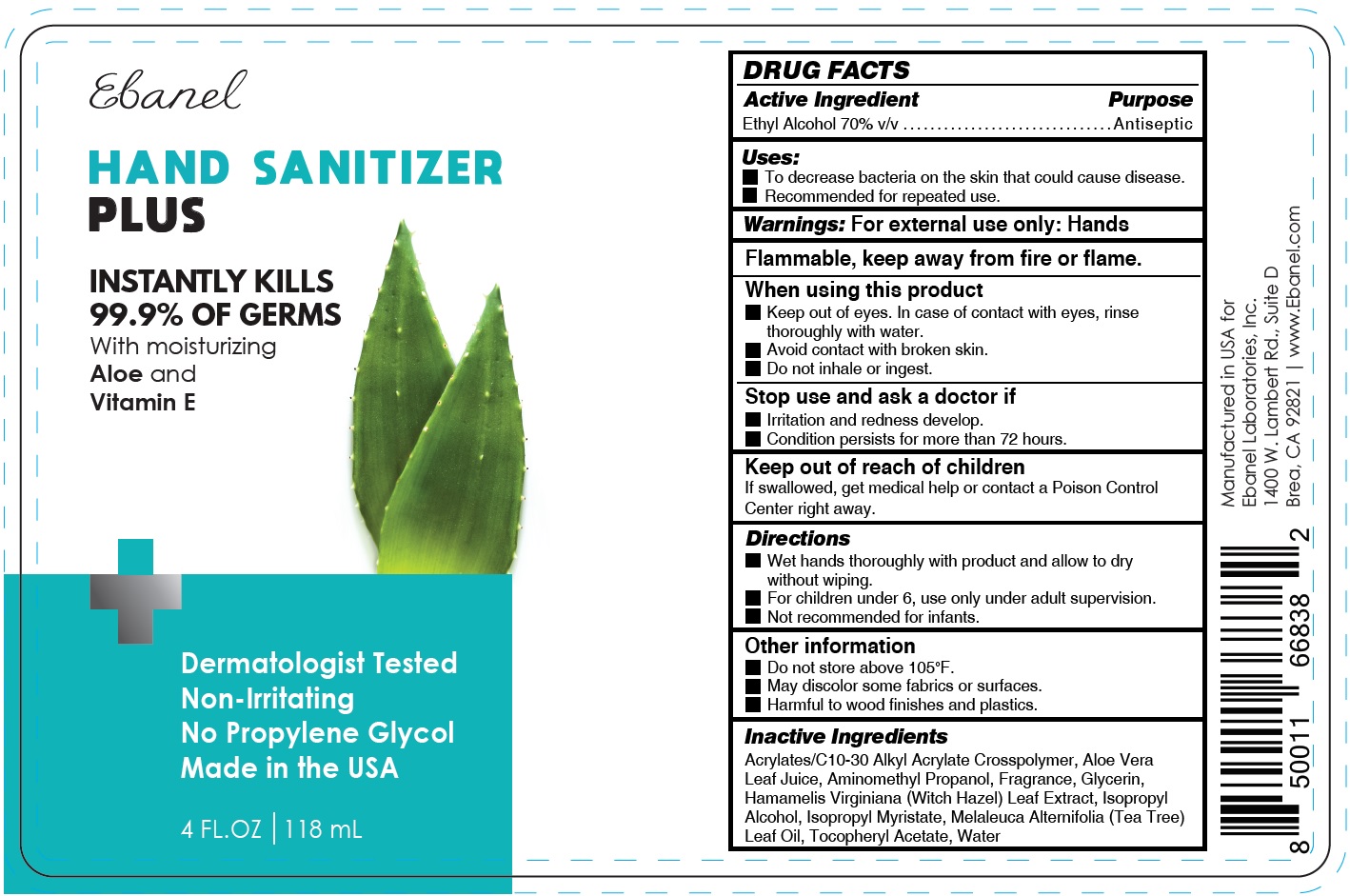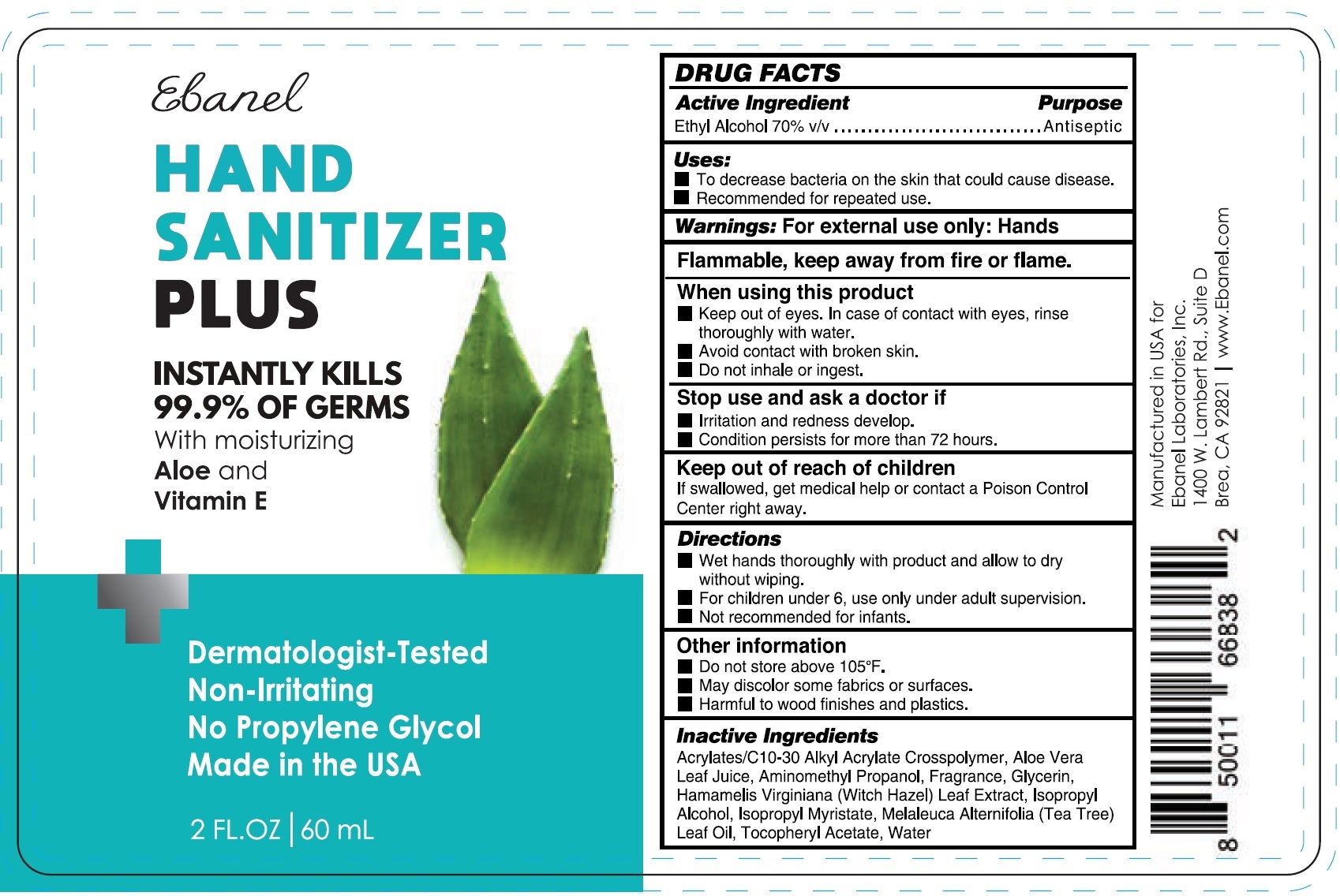 DRUG LABEL: Hand Sanitizer Plus
NDC: 63742-040 | Form: GEL
Manufacturer: Clinical Resolution Laboratory, Inc.
Category: otc | Type: HUMAN OTC DRUG LABEL
Date: 20231226

ACTIVE INGREDIENTS: ALCOHOL 0.7 mL/1 mL
INACTIVE INGREDIENTS: CARBOMER INTERPOLYMER TYPE A (ALLYL SUCROSE CROSSLINKED); ALOE VERA LEAF; AMINOMETHYLPROPANOL; GLYCERIN; HAMAMELIS VIRGINIANA LEAF; ISOPROPYL ALCOHOL; ISOPROPYL MYRISTATE; TEA TREE OIL; .ALPHA.-TOCOPHEROL ACETATE; WATER

Hand Sanitizer Plus

Active Ingredient

Ethyl Alcohol 70% v/v

Purpose

Antiseptic

Uses:

- To decrease bacteria on the skin that could cause disease.
- Recommended for repeated use.

Warnings:

For external use only: Hands

Flammable, keep away from fire or flame.

When using this product

- Keep out of eyes. In case of contact with eyes, rinse thoroughly with water.
- Avoid contact with broken skin.
- Do not inhale or ingest.

Stop use and ask a doctor if

- Irritation and redness develop.
- Condition persists for more than 72 hours.

Keep out of reach of children

If swallowed, get medical help or contact a Poison Control Center right away.

Directions

- Wet hands thoroughly with product and allow to dry without wiping.
- For children under 6, use only under adult supervision.
- Not recommended for infants.

Other information

- Do not store above 105°F.
- May discolor some fabrics or surfaces.
- Harmful to wood finishes and plastics.

Inactive Ingredients

Acrylates/C10-30 Alkyl Acrylate Crosspolymer, Aloe Vera Leaf Juice, Aminomethyl Propanol, Fragrance, Glycerin, Hamamelis Virginiana (Witch Hazel) Leaf Extract, Isopropyl Alcohol, Isopropyl Myristate, Melaleuca Alternifolia (Tea Tree) Leaf Oil, Tocopheryl Acetate, Water